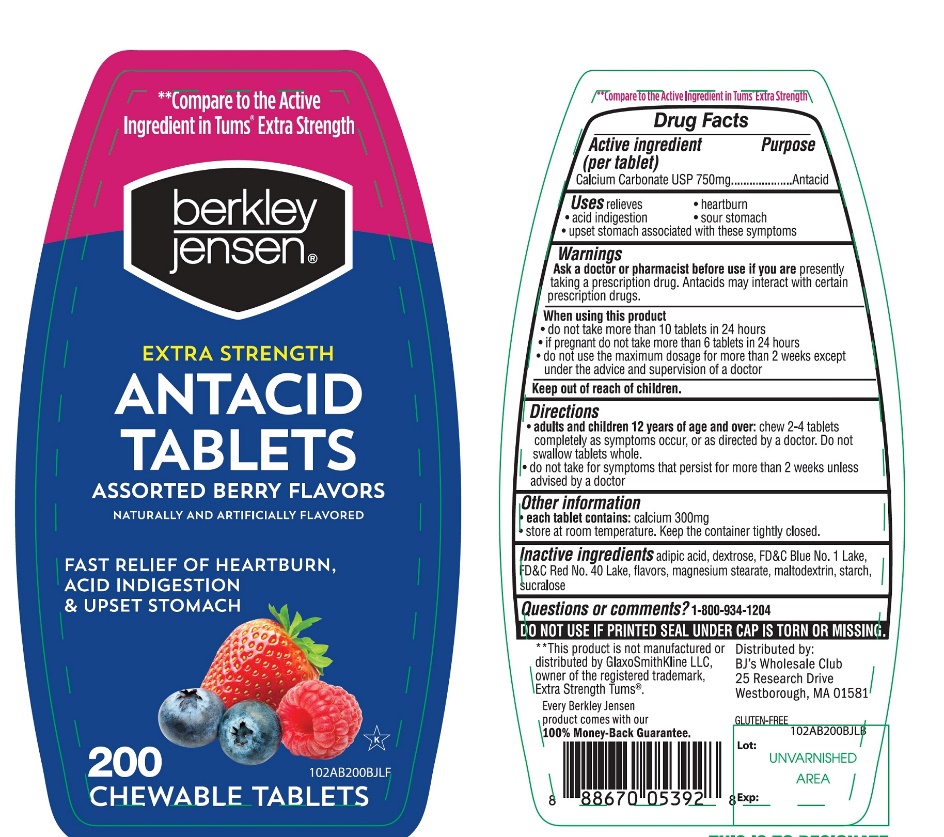 DRUG LABEL: Extra Strength

NDC: 68391-102 | Form: TABLET, CHEWABLE
Manufacturer: BJWC
Category: otc | Type: HUMAN OTC DRUG LABEL
Date: 20250718

ACTIVE INGREDIENTS: CALCIUM CARBONATE 750 mg/1 1
INACTIVE INGREDIENTS: ADIPIC ACID; DEXTROSE, UNSPECIFIED FORM; FD&C BLUE NO. 1; FD&C RED NO. 40; MAGNESIUM STEARATE; MALTODEXTRIN; STARCH, CORN; SUCRALOSE

Extra Strength Antacid 200 Chewable Tablets Drug Facts

Active ingredient (per tablet)

Calcium Carbonate USP 750mg

Purpose

Antacid

Uses

relieves

- heartburn
- acid indigestion
- sour stomach
- upset stomach associated with these symptoms

Ask a doctor or pharmacist before use if you are

presently taking a prescription drug. Antacids may interact with certain prescription drugs.

When using this product

- do not take more than 10 tablets in 24 hours
- if pregnant do not take more than 6 tablets in 24 hours
- do not use the maximum dosage for more than 2 weeks except under the advice and supervision of a doctor

Directions

- adults and children 12 years of age and over:chew 2-4 tablets as symptoms occur, or as directed by a doctor. Do not swallow tablets whole.
- do not take for symptoms that persist for more than 2 weeks unless advised by a doctor

Other information

- each tablet contains: elemental calcium 300mg
- store at room temperature. Keep the container tightly closed.

Inactive Ingredients

adipic acid, dextrose, FD&C blue #1 lake, FD&C red # 40 lake, flavor, magnesium stearate, maltodextrin, starch, sucralose.

Questions or comments?

1-866-467-2748

Safety Sealed

DO NOT USE IF PRINTED SEAL UNDER CAP IS TORN OR MISSING

Package/Label Principal Display Panel

berkley jensen®

NDC# 68391-102-00

**Compare to the Active Ingredient in TUMs®Extra Strength

Extra Strength

ANTACID TABLETS

ASSORTED BERRY FLAVORS

FAST RELIEF OF:

- ACID INDIGESTION
- UPSET STOMACH
- HEARTBURN

200 CHEWABLE TABLETS

K PAREVE

Every Berkley Jensen product comes with our

100% Money-Back Guarantee.

Distributed by:

BJ’S Wholesale Club,

25 Research Drive,

Westborough, MA 01581.

Questions? 1-800-934-1204

Made in USA

*This product is not manufactured or distributed by GlaxoSmithKline LLC, owner of the registered trademark, Extra Strength Tums®.